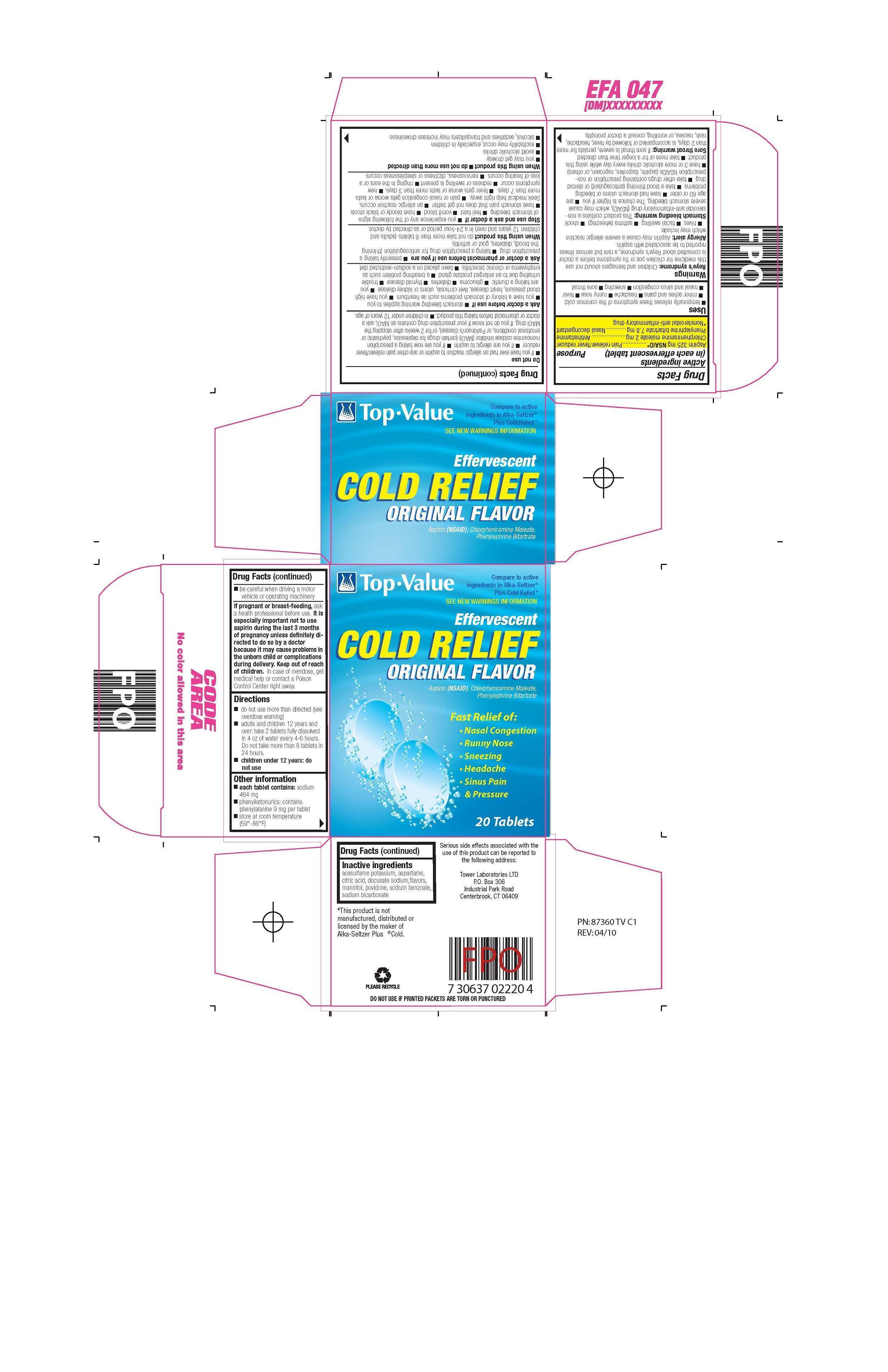 DRUG LABEL: Effervescent Cold Relief  
NDC: 50201-0246 | Form: TABLET, EFFERVESCENT
Manufacturer: Tower Laboratories Ltd
Category: otc | Type: HUMAN OTC DRUG LABEL
Date: 20120831

ACTIVE INGREDIENTS: ASPIRIN 325 mg/1 1; CHLORPHENIRAMINE MALEATE 2 mg/1 1; PHENYLEPHRINE BITARTRATE 7.8 mg/1 1
INACTIVE INGREDIENTS: ACESULFAME POTASSIUM; ASPARTAME; CITRIC ACID MONOHYDRATE; DOCUSATE SODIUM; MANNITOL; POVIDONE K30; SODIUM BENZOATE; SODIUM BICARBONATE

Drug Facts

Active Ingredients (in each effervescent tablet) Purpose

Aspirin 325 mg NSAID*.......................................... Pain reliever/fever reducer
Chlorpheniramine maleate 2 mg ............................... Antihistamine
Phenylephrine Bitartrate 7.8 mg ............................... Nasal decongestant

*Nonsteroidal anti-inflammatory drug

Warnings

Reye's syndrome: Children and teenagers should not use this drug for chicken pox or flu symptoms before a doctor is consulted about Reye's syndrome, a rare but serious illness reported to be associated with aspirin.

Allergy alert: Aspirin may cause a server allergic reaction which may include: - hives - facial swelling - asthma (wheezing) - shock

Stomach bleeding warning: This product contains a nonsteroidal anti-inflammatory drug (NSAID), which may cause severe stomach bleeding. The chance is higher if you - are age 60 or older - have had stomach ulcers or bleeding problems - take a blood thinning (anticoagulant) or steroid drug - take other drugs containing prescription or nonprescription NSAIDs (aspirin, ibuprofen, naproxen, or others) - have 3 or more alcoholic drinks every day while using this product - take more or for a longer time than directed.

Sore throat warning: If sore throat is severe, persists for more than 2 days, is accompanied or followed by fever, headache, rash, nausea, or vomiting, consult a doctor promptly.

Ask a doctor before use if - stomach bleeding warning applies to you - you have a history of stomach problems, such as heartburn - you have high blood pressure, heart disease, liver cirrhosis, or kidney disease - glaucome - diabetes - thyroid disease - trouble urinating due to an enlarged prostate gland - a breathing problem such as emphysema or chronic bronchitis - you are taking a diuretic - been placed on a sodium-restricted diet.

Ask a doctor or pharmacist before use if you are:

- presently taking a prescription drug.
- taking a prescription drug for anticoagulation (thinning the blood), diabetes, gout or arthritis.

Do not use - if you have ever had an allergic reaction to any other pain reliever/fever reducer - if you are allergic to aspirin - if you are now taking a prescription monoamine oxidase inhibitor (MAOI) (certain drugs for depression, psychiatric or emotional conditions, or Parkinson's disease), or for 2 weeks after stopping the MAOI drug. If you do not know if your prescription drug contains an MAOI, ask a doctor or pharmacist before taking this product.

Keep out of reach of children. In case of overdose, get medical help or contact a Poison Control Center right away.

PREGNANCY OR BREAST FEEDING

If pregnant or breast-feeding, ask a health professional before use. It is especially important not to use aspirin during the last 3 months of pregnancy unless definitely directed to do so by a doctor because it may cause problems in the unborn child or complications during delivery.

PURPOSE

Fast Relief of: Nasal Congetion, Runny Nose, Sneezing, Headache, Sinus Pain and Pressure

INDICATIONS AND USAGE

Uses: temporarily relieves these symptoms of the common cold:

- fever - sneezing - nasal congestion - sore throat - headache - minor aches and pains - runny nose - sinus congestion and pressure

Stop use and ask a doctor if - you experience any of the following signs of stomach bleeding - feel faint - vomit blood - have bloody stools - have stomach pain that does not get better - an allergic reaction occurs, seek medical help right away. - pain or nasal congestion gets worse or lasts more than 7 days. - fever gets worse or lasts more than 3 days. - new symptoms occur - redness or swelling is present - ringing in the ears or loss of hearing occurs - nervousness, dizziness or sleeplessness occurs.

When using this product:

- do not take more than 8 tablets (adults and children 12 years and over) in a 24-hour period or as directed by a doctor.
- do not use more than directed
- you may get drowsy
- avoid alcoholic drinks
- excitability may occur, especially in children
- alcohol, sedatives and tranquilizers may increase drowsiness
- be careful when driving a motor vehicle or operating machinery

ADVERSE REACTIONS

Adverse Event Reporting: Serious side effects associated with the use of this product can be reported to the following address or by calling the following telephone number.

Directions

- do not use more than directed (see overdose warning)
- adults and children 12 years and over: take 2 tablets completely dissolved in 4 ounces of water every 4-6 hours
- do not take more than 8 tablets in 24 hours

- children under 12 years: ask a doctor

Inactive ingredients:

acesulfame potassium, aspartame, citric acid, docusate sodium, mannitol, povidone, sodium benzoate, sodium bicarbonate